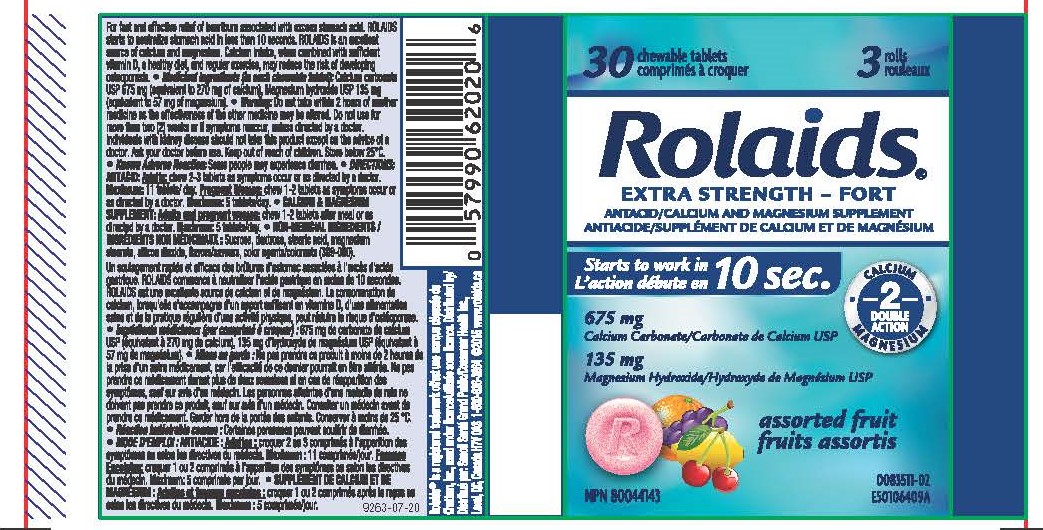 DRUG LABEL: Calcium Carbonate, Magnesium Hydroxide
NDC: 10267-0013 | Form: TABLET, CHEWABLE
Manufacturer: Contract Pharmacal Corp.
Category: otc | Type: HUMAN OTC DRUG LABEL
Date: 20210111

ACTIVE INGREDIENTS: CALCIUM CARBONATE 675 mg/1 1; MAGNESIUM HYDROXIDE 135 mg/1 1
INACTIVE INGREDIENTS: ORANGE; STEARIC ACID; DEXTROSE; CHERRY; MALTODEXTRIN; FD&C YELLOW NO. 6; LEMON; SILICON DIOXIDE; SUCRALOSE; FD&C YELLOW NO. 5; FD&C BLUE NO. 1; MAGNESIUM STEARATE; SUCROSE; GRAPE; FD&C RED NO. 40

4400- Export